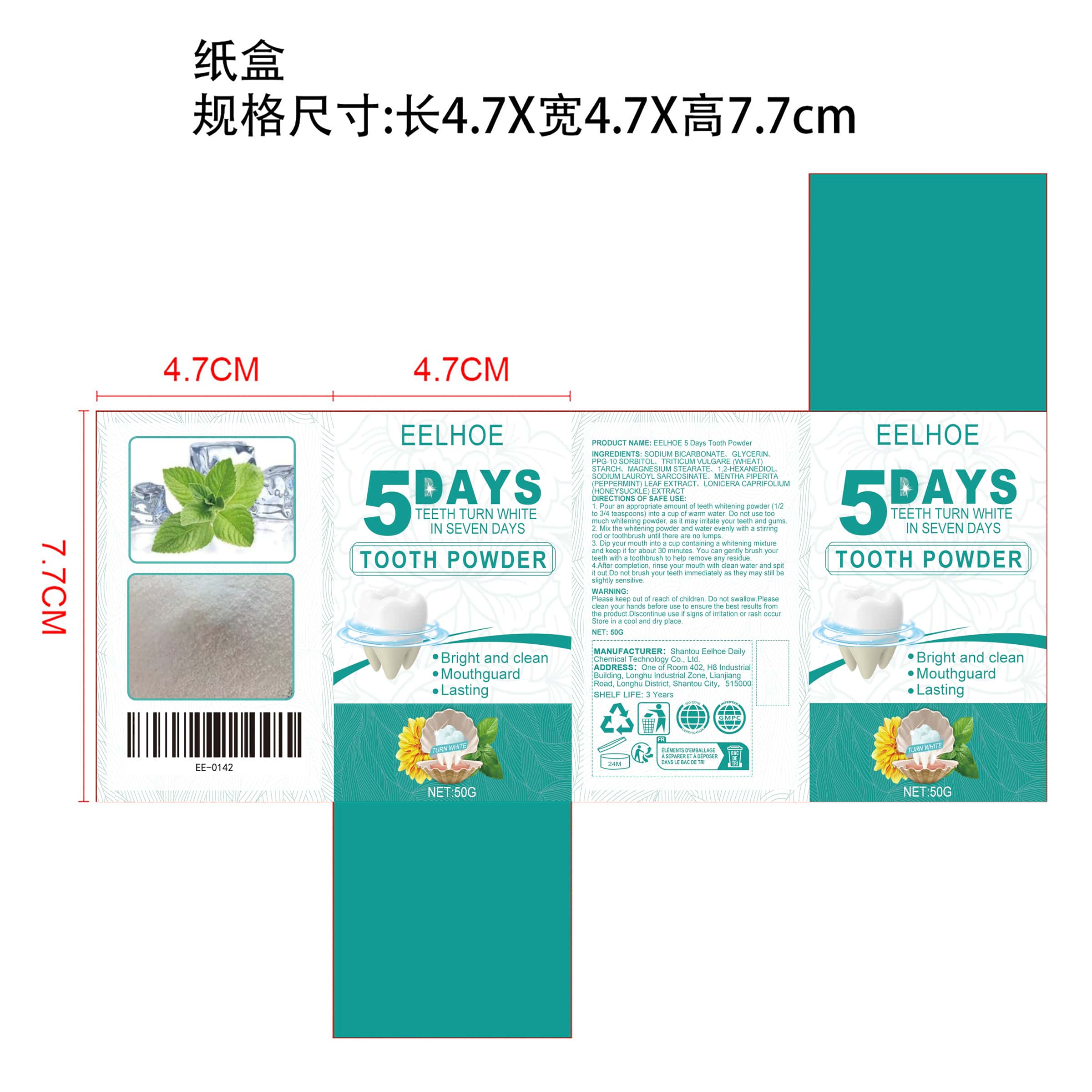 DRUG LABEL: EELHOE 5 Days Tooth Powder
NDC: 85064-018 | Form: POWDER, DENTIFRICE
Manufacturer: Shantou Eelhoe Daily Chemical Technology Co., Ltd.
Category: otc | Type: HUMAN OTC DRUG LABEL
Date: 20251127

ACTIVE INGREDIENTS: MENTHA PIPERITA (PEPPERMINT) LEAF 0.01 mg/50 mg; LONICERA CAPRIFOLIUM WHOLE 0.01 mg/50 mg
INACTIVE INGREDIENTS: 1,2-HEXANEDIOL 0.25 mg/50 mg; SODIUM LAUROYL SARCOSINATE 0.25 mg/50 mg; SORBITOL 2 mg/50 mg; GLYCERIN 3 mg/50 mg; MAGNESIUM STEARATE 1.5 mg/50 mg; SODIUM BICARBONATE 41.48 mg/50 mg; WHEAT SPROUT 1.5 mg/50 mg

ACTIVE INGREDIENT

MENTHA PIPERITA (PEPPERMINT) LEAF EXTRACT、LONICERA CAPRIFOLIUM (HONEYSUCKLE) EXTRACT

PURPOSE

Bright and clean
Mouthguard
Lasting

WHEN USING

1. Pour an appropriate amount of teeth whitening powder (1/2 to 3/4 teaspoons) into a cup of warm water. Do not use too much whitening powder, as it may irritate your teeth and gums.

2. Mix the whitening powder and water evenly with a stirring rod or toothbrush until there are no lumps.

3. Dip your mouth into a cup containing a whitening mixture and keep it for about 30 minutes. You can gently brush your teeth with a toothbrush to help remove any residue.

4. After completion, rinse your mouth with clean water and spit it out. Do not brush your teeth immediately as they may still be slightly sensitive.

WARNINGS

Please keep out of reach of children. Do not swallow.Please clean your hands before use to ensure the best results from the product. Discontinue use if signs of irritation or rash occur. Store in a cool and dry place.

DO NOT USE

Discontinue use if signs of irritation or rash occur.

STOP USE

Discontinue use if signs of irritation or rash occur.

KEEP OUT OF REACH OF CHILDREN

Please keep out of reach of children. Do not swallow.

STORAGE AND HANDLING

Store in a cool and dry place.

INACTIVE INGREDIENT

SODIUM BICARBONATE、GLYCERIN、PPG-10 SORBITOL、TRITICUM VULGARE (WHEAT) STARCH、MAGNESIUM STEARATE、1,2-HEXANEDIOL、SODIUM LAUROYL SARCOSINATE

INDICATIONS AND USAGE

1. Pour an appropriate amount of teeth whitening powder (1/2 to 3/4 teaspoons) into a cup of warm water. Do not use too much whitening powder, as it may irritate your teeth and gums.

2. Mix the whitening powder and water evenly with a stirring rod or toothbrush until there are no lumps.

3. Dip your mouth into a cup containing a whitening mixture and keep it for about 30 minutes. You can gently brush your teeth with a toothbrush to help remove any residue.

4. After completion, rinse your mouth with clean water and spit it out. Do not brush your teeth immediately as they may still be slightly sensitive.

DOSAGE AND ADMINISTRATION

1. Pour an appropriate amount of teeth whitening powder (1/2 to 3/4 teaspoons) into a cup of warm water. Do not use too much whitening powder, as it may irritate your teeth and gums.

2. Mix the whitening powder and water evenly with a stirring rod or toothbrush until there are no lumps.

3. Dip your mouth into a cup containing a whitening mixture and keep it for about 30 minutes. You can gently brush your teeth with a toothbrush to help remove any residue.

4. After completion, rinse your mouth with clean water and spit it out. Do not brush your teeth immediately as they may still be slightly sensitive.